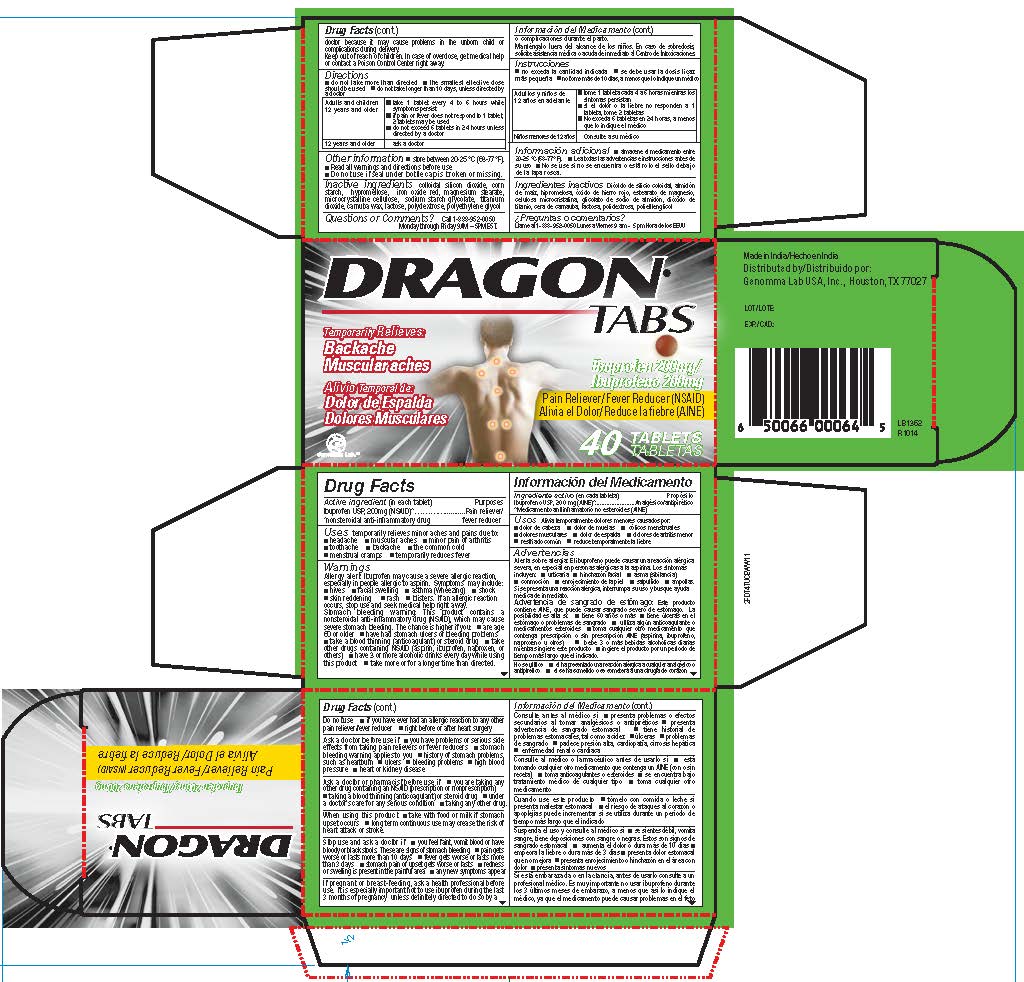 DRUG LABEL: Dragon
NDC: 50066-374 | Form: TABLET
Manufacturer: Genomma Lab USA
Category: otc | Type: HUMAN OTC DRUG LABEL
Date: 20150417

ACTIVE INGREDIENTS: IBUPROFEN 200 mg/1 1
INACTIVE INGREDIENTS: SILICON DIOXIDE; STARCH, CORN; HYPROMELLOSES; FERRIC OXIDE RED; MAGNESIUM STEARATE; CELLULOSE, MICROCRYSTALLINE; SODIUM STARCH GLYCOLATE TYPE A CORN; TITANIUM DIOXIDE; LACTOSE; POLYDEXTROSE; POLYETHYLENE GLYCOLS

Drug Facts

Active ingredient

Ibuprofen USP, 200mg (NSAID)**
**nonsteroidal anti-inflammatory drug

Purpose

Pain reliever/fever reducer

Uses

temporarily relieves minor aches and pains due to: ■ headache ■ muscular aches ■ minor pain of arthritis ■ toothache ■ backache ■ the common cold ■ menstrual cramps ■ temporarily reduces fever

Warnings

Allergy alert: Ibuprofen may cause a severe allergic reaction, especially in people allergic to aspirin. Symptoms may include: ■ hives ■ facial swelling ■ asthma (wheezing) ■ shock■ skin reddening
■ rash ■ blisters
If an allergic reaction occurs, stop use and seek medical help right away.
Stomach bleeding warning:This product contains a nonsteroidal anti-inflammatory drug (NSAID), which may cause severe stomach bleeding. The chances are higher if you: ■ are age 60 or older ■ have had stomach ulcers or bleeding problems ■ take a blood thinning (anticoagulant) or steroid drug ■ take other drugs containing prescription or nonprescription NSAIDs (aspirin, ibuprofen, naproxen, or others) ■ have 3 or more alcoholic drinks every day while using this product ■ take more or for a longer time than directed.

Do not use

if you have ever had an allergic reaction to any other pain reliever/fever reducer ■ right before or
after heart surgery

Ask a doctor before use if

■ you have problems or serious side effects from taking pain relievers or fever reducers ■ the stomach bleeding warning applies to you■ you have a history of stomach problems, such as heartburn ■ you
have high blood pressure, heart disease, liver cirrhosis, or kidney disease ■ you have asthma ■ you are taking a diuretic

Ask a doctor or pharmacist before use if

you are taking any other drug containing an NSAID (prescription or nonprescription) taking a
blood thinning (anticoagulant) or steroid drug under a doctor’s care for any serious condition
taking any other drug

When using this product

take with food or milk if stomach upset occurs
long term continuous use may increase the risk of heart attack or stroke

Stop use and ask a doctor if

you faint, vomit blood, have bloody or black stools. These are signs of stomach bleeding. pain gets worse or lasts more than 10 days ■ fever gets worse or lasts more than 3 days stomach pain or upset gets worse or lasts redness or swelling is present in the painful area any new symptoms appear

If pregnant or breast-feeding

ask a health professional before use. It is especially important not to use ibuprofen during the last 3 months of pregnancy unless definitely directed to do so by a doctor because it may cause problems in the unborn child or complications during delivery.

Keep Out of Reach of Children

In case of overdose, get medical help or contact a Poison Control Center right away (1-800-222-1222).

Directions

■ do not take more than directed
■ the smallest effective dose should be used
■ do not take longer than 10 days, unless directed by a doctor (see Warnings)
Adults and children 12 years and older: ■ take 1 tablet every 4 to 6 hours while symptoms persist
■ if pain or fever does not respond to 1 tablet, 2 tablets may be used ■ do not exceed 6 tablets in
24 hours unless directed by a doctor
Children under 12 years:ask a doctor

Other information

store between 20-25 °C (68-77° F).■ Read all warnings and directions before useDo not use if
seal under bottle cap is broken or missing.

Inactive Ingredients

colloidal silicon dioxide, corn starch, hypromellose, iron oxide red, magnesium stearate,
microcrystalline cellulose, sodium starch glycolate, titanium dioxide, carnuba wax, lactose, polydextrose, polyethylene glycol

Questions or Comments?

Call 1-888-952-0050 Monday through Friday 9AM – 5PM EST.

Package/Label Principal Display Panel

Dragon Tabs
Ibuprofen 200 mg/Ibuprofeno 200mg
Pain Reliever/Fever Reducer (NSAID)
Alivia el Dolor/Reduce la fiebre (AINE)

Temporarily Relieves:
Backache
Muscular aches
Alivio Temporal de:
Dolor de Espalda
Dolores Musculares

40 Tablets/Tabletas